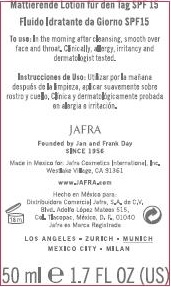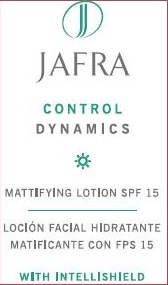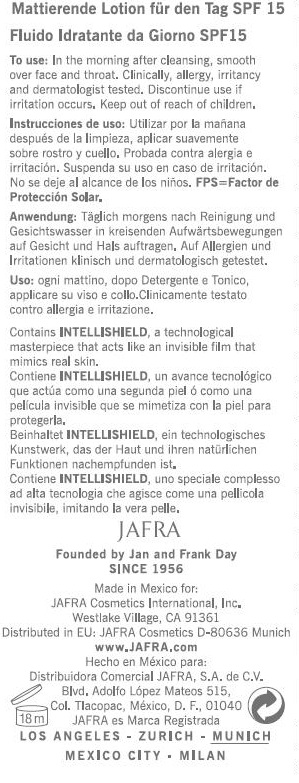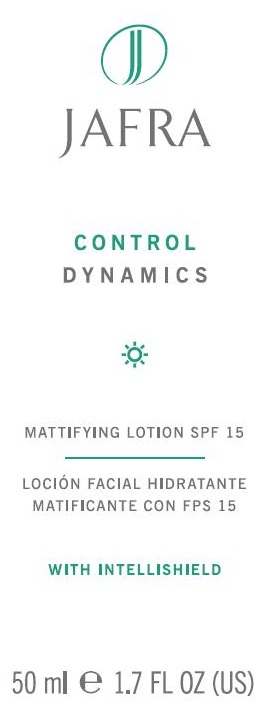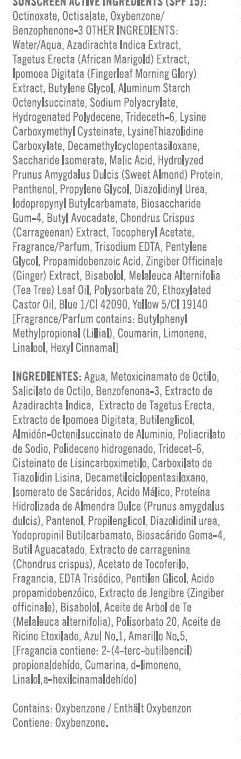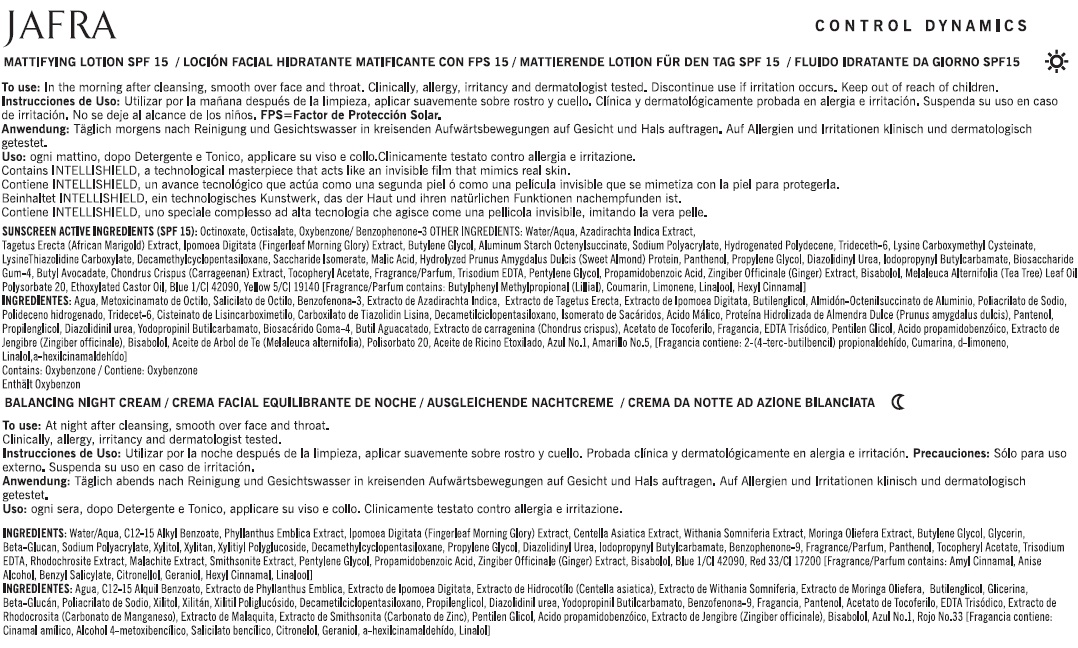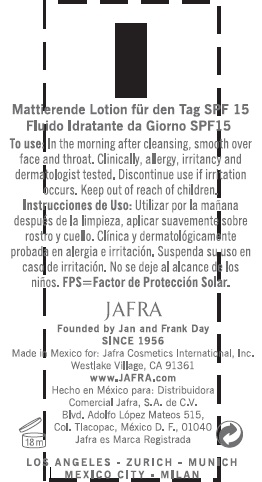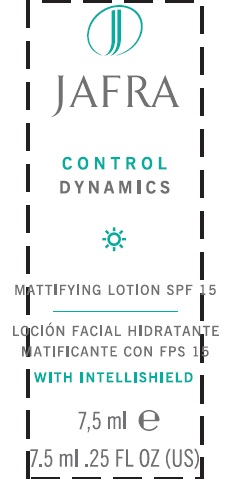 DRUG LABEL: CONTROL DYNAMICS MATTIFYING
NDC: 68828-158 | Form: LOTION
Manufacturer: JAFRA COSMETICS INTERNATIONAL
Category: otc | Type: HUMAN OTC DRUG LABEL
Date: 20120531

ACTIVE INGREDIENTS: OCTINOXATE 7 g/100 mL; OCTISALATE 4 g/100 mL; OXYBENZONE 2 g/100 mL
INACTIVE INGREDIENTS: WATER; AZADIRACHTA INDICA BARK; TAGETES ERECTA FLOWER; IPOMOEA MAURITIANA TUBER; BUTYLENE GLYCOL; ALUMINUM STARCH OCTENYLSUCCINATE; SODIUM POLYACRYLATE (8000 MW); HYDROGENATED POLYDECENE (550 MW); TRIDECETH-6; CYSTEINE, DL-; LYSINE HYDROCHLORIDE; CYCLOMETHICONE 5; SACCHARIDE ISOMERATE; MALIC ACID; ALMOND; PANTHENOL; PROPYLENE GLYCOL; DIAZOLIDINYL UREA; IODOPROPYNYL BUTYLCARBAMATE; BIOSACCHARIDE GUM-1; PERSEA AMERICANA LEAF; CHONDRUS CRISPUS; .ALPHA.-TOCOPHEROL ACETATE; EDETATE TRISODIUM; PENTYLENE GLYCOL; HYDROXYPHENYL PROPAMIDOBENZOIC ACID; GINGER; LEVOMENOL; TEA TREE OIL; POLYSORBATE 20; POLYOXYL 60 CASTOR OIL; FD&C BLUE NO. 1; FD&C YELLOW NO. 5

CONTROL DYNAMICS MATTIFYING LOTION SPF 15

SUNSCREEN ACTIVE INGREDIENT (SPF 15):
OCTINOXATE, OCTISALATE, OXYBENZONE/BENZOPHENONE-3

PURPOSE: SUNSCREEN

INACTIVE INGREDIENT

OTHER INGREDIENTS: WATER/AQUA, AZADIRACHTA INDICA EXTRACT, TAGETUS ERECTA (AFRICN MARIGOLD) EXTRACT, IPOMOEA DIGITATA (FINGERLEAF MORNING GLORY) EXTRACT, BUTYLENE GLYCOL, ALUMINUM STARCH OCTENYLSUCCINATE, SODIUM POLYACRYLATE, HYDROGENATED POLYDECENE, TRIDECETH-6, LYSINE CARBOXYMETHYL CYSTEINATE, LYSINE THIAZOLIDINE CARBOXYLATE, DECAMETHYLCYCLOPENTASILOXANE, SACCHARIDE ISOMERATE, MALIC ACID, HYDROLYZED PRUNUS AMGDALUS DULCIS (SWEET ALMOND) PROTEIN, PANTHENOL, PROPYLENE GLYCOL, DIAZOLIDINYL UREA, IODOPROPYNYL BUTYLCARBAMATE, BIOSACCHARIDE GUM-4, BUTYL AVOCADATE, CHONDRUS CRISPUS, (CARRAGEENAN) EXTRACT, TOCOPHERYL ACETATE, FRAGRANCE/PARFUM, TRISODIUM EDTA, PENTYLENE GLYCOL, PROPAMIDOBENZOIC ACID, ZINGIBER OFFICINALE (GINGER) EXTRACT, BISABOLOL, MELALEUCA ALTERNIFOLIA (TEA TREE) LEAF OIL, POLYSORBATE 20, ETHOXYLATED CASTOR OIL, BLUE 1/CI 42090, YELLOW 5/CI 19140 [FRAGRANCE/PARFUM CONTAINS: BUTYLPHENYL METHYLPROPIONAL (LILLIAL), COUMARIN, LIMONENE, LINALOOL, HEXYL CINNAMAL]

INDICATIONS AND USAGE

MATTIFYING LOTION SPF 15

INSTRUCTIONS FOR USE

TO USE: IN THE MORNING AFTER CLEANSING, SMOOTH OVER FACE AND THROAT.

WARNINGS

CAUTION: FOR EXTERNAL USE ONLY. AVOID CONTACT WITH EYES.

DISCONTINUE USE IF IRRITATION OCCUR.

KEEP OUT OF REACH OF CHILDREN.

PACKAGE LABEL

JAFRA

CONTROL DYNAMICS

MATTIFYING LOTION SPF 15